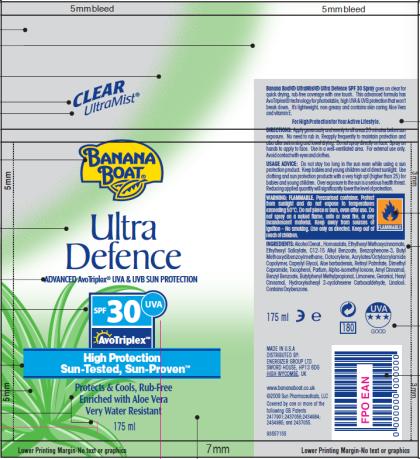 DRUG LABEL: Banana Boat Ultra Defence SPF 30 for UK
NDC: 17630-2022 | Form: SPRAY
Manufacturer: Accra-Pac, Inc.
Category: otc | Type: HUMAN OTC DRUG LABEL
Date: 20100326

ACTIVE INGREDIENTS: HOMOSALATE 0.0878 mL/1 mL; OCTINOXATE 0.05 mL/1 mL; OCTISALATE 0.05 mL/1 mL; OCTOCRYLENE 0.025 mL/1 mL; OXYBENZONE 0.05 mL/1 mL; AVOBENZONE 0.03 mL/1 mL
INACTIVE INGREDIENTS: C12-15 ALKYL BENZOATE; CAPRYLYL GLYCOL; ALOE VERA LEAF; VITAMIN A PALMITATE; BENZYL BENZOATE; LIMONENE, DL-; GERANIOL; LINALOOL, DL-

Banana Boat Ultra Defence SPF 30 for UK

Active Ingredients

Homosalate 0.0878mL / 1mL

Octinoxate 0.05mL / 1mL

Octisalate 0.05mL / 1mL

Octocrylene 0.025mL / 1mL

Oxybenzone 0.05mL / 1mL

Avobenzone 0.03mL / 1mL

DIRECTIONS:

Apply generously and evenly to all areas 20 minutes before sun exposure. No need to rub in. Reapply frequently to maintain protection and also after swimming and towel drying. Do not spray directly on face. Spray on hands to apply to face. Use in a well-ventilated area. For external use only. Avoid contact with eyes and clothes.

USAGE ADVICE:

Do not stay too long in the sun even while using a sun protection product. Keep babies and young children out of direct sunlight. Use clothing and sun protection products with a very high spf (higher than 25) for babies and young children. Over exposure to the sun is a serious health threat. Reducing applied quantity will significantly lower the level of protection.

WARNING:

FLAMMABLE. Pressurised container. Protect from sunlight and do not expose to temperatures exceeding 50°C. Do not pierce or burn, even after use. Do not spray on a naked flame, onto or near fire, or any incandescent material. Keep away from sources of ignition – No smoking. Use only as directed.

INGREDIENTS:

Alcohol Denat., Homosalate, Ethylhexyl Methoxycinnamate, Ethylhexyl Salicylate, C12-15 Alkyl Benzoate, Benzophenone-3, Butyl Methoxydibenzoylmethane, Octocrylene, Acrylates/Octylacrylamide Copolymer, Caprylyl Glycol, Aloe barbadensis, Retinyl Palmitate, Dimethyl Capramide, Tocopherol, Parfum, Alpha-isomethyl Ionone, Amyl Cinnamal, Benzyl Benzoate, Butylphenyl Methylpropional, Limonene, Geraniol, Hexyl Cinnamal, Hydroxyisohexyl 3-cyclohexene Carboxaldehyde, Linalool.

Contains Oxybenzone.

MADE IN U.S.A
DISTRIBUTED BY:
ENERGIZER GROUP LTD
SWORD HOUSE, HP13 6DG
HIGH WYCOMBE, UK
www.bananaboat.co.uk

PRINCIPAL DISPLAY PANEL

CLEAR
UltraMist®
BANANA
BOAT®
Ultra
Defence
ADVANCED AvoTriplex® UVA & UVB SUN PROTECTION
SPF 30 UVA
Avotriplex TM
High Protection
Sun-Tested, Sun-Proven TM
Protects & Cools, Rub-Free
Enriched with Aloe Vera
Very Water Resistant
175 ml